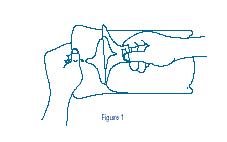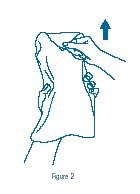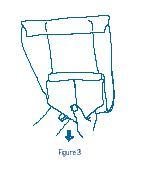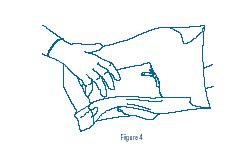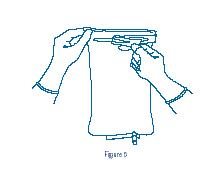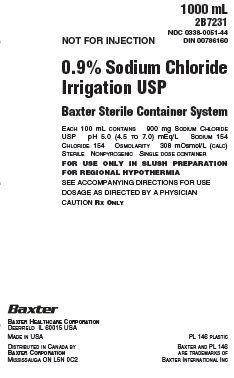 DRUG LABEL: Sodium Chloride
NDC: 0338-0051 | Form: IRRIGANT
Manufacturer: Baxter Healthcare Corporation
Category: prescription | Type: HUMAN PRESCRIPTION DRUG LABEL
Date: 20180402

ACTIVE INGREDIENTS: SODIUM CHLORIDE 9 g/1000 mL
INACTIVE INGREDIENTS: WATER

0.9% Sodium Chloride Irrigation, USP
Baxter Sterile Container System

DESCRIPTION

0.9% Sodium Chloride Irrigation, USP in the Baxter Sterile Container System is a sterile, nonpyrogenic, isotonic solution for the preparation of slushed solution. It contains no antimicrobial agents. Composition, osmolarity, pH and ionic concentration are shown in Table 1.

Table 1
 | Size (mL) | Composition (g/L) | Osmolarity (mOsmol/L) (calc) | pH | Ionic Concentration (mEq/L)
 | Size (mL) | Sodium Chloride, USP (NaCl) | Osmolarity (mOsmol/L) (calc) | pH | Sodium | Chloride
0.9 % Sodium Chloride Irrigation, USP | 1000 | 9 | 308 | 5.0 (4.5 to 7.0) | 154 | 154

The Baxter Sterile Container System is designed to provide a slush container with a sterile exterior surface for use within the surgical field. Within the overwrap, the unit is packaged in a dispensing bag which maintains the sterility of this surface.

The flexible plastic slush container is fabricated from a specially formulated polyvinyl chloride (PL 146 Plastic). The amount of water that can permeate from inside the container into the overwrap is insufficient to affect the solution significantly. Solutions in contact with the plastic container can leach out certain of its chemical components in very small amounts within the expiration period, e.g., di-2-ethylhexyl phthalate (DEHP), up to 5 parts per million. However, the safety of the plastic has been confirmed in tests in animals according to USP biological tests for plastic containers as well as by culture toxicity studies.

CLINICAL PHARMACOLOGY

Slushed solution is used to induce regional hypothermia in conditions such as certain open heart and kidney surgical procedures by direct application of slushed solution. The objective of regional hypothermia is to reduce cellular metabolic activity so that body tissues can tolerate a period of total or relative ischemia thereby inhibiting the formation and buildup of destructive autolytic enzymes and anaerobic by-products usually produced and accumulated in ischemic tissues.

INDICATIONS AND USAGE

Slushed solution is used to create regional hypothermia in order to reduce and minimize manifestations of warm-temperature ischemia. Temperature probes may be used to determine requirements for replacement or addition of slushed solution.

CONTRAINDICATIONS

None known

WARNINGS

Not for injection. For use in slush preparation for regional hypothermia.

PRECAUTIONS

General Precautions

Avoid prolonged direct contact between ice crystals and body tissues.

Experience in use of slushed solutions in pediatrics is limited.

Carcinogenesis, Mutagenesis, Impairment of Fertility

Studies performed with slushed 0.9% Sodium Chloride Irrigation, USP have not been performed to evaluate carcinogenic potential, mutagenic potential, or effects on fertility.

Pregnancy

Teratogenic Effects

Animal reproduction studies have not been conducted with slushed 0.9% Sodium Chloride Irrigation, USP. It is also not known whether slushed 0.9% Sodium Chloride Irrigation, USP can cause fetal harm when administered to a pregnant woman or can affect reproduction capacity. Slushed 0.9% Sodium Chloride Irrigation, USP should be given to a pregnant woman only if clearly needed.

Nursing Mothers

It is not known whether this drug is excreted in human milk. Because many drugs are excreted in human milk, caution should be exercised when slushed 0.9% Sodium Chloride Irrigation, USP is administered to a nursing mother.

Pediatric Use

Safety and effectiveness of slushed 0.9% Sodium Chloride Irrigation, USP in pediatric patients have not been established by adequate and well controlled trials; however, the use of electrolyte solutions in the pediatric population is referenced in the medical literature. The warnings, precautions and adverse reactions identified in the label copy should be observed in the pediatric population.

Do not administer unless seals of outer dispensing bag are intact.

ADVERSE REACTIONS

No serious adverse reactions are known.

DOSAGE AND ADMINISTRATION

The volume of slushed solution required will vary with patient’s age, clinical condition, cooling effect desired and duration of cooling effect desired, according to physician’s instructions.

HOW SUPPLIED/STORAGE AND HANDLING

.9% Sodium Chloride Irrigation, USP in the Baxter Sterile Container System is supplied as follows:

Code | Size (mL) | NDC | DIN
2B7231 | 1000 | 0338-0051-44 | 786160

Exposure of pharmaceutical products to heat should be minimized. Avoid excessive heat. Avoid freezing except during controlled slushing procedure. It is recommended that this product be stored at room temperature (25ºC); brief exposure up to 40ºC does not adversely affect this product.

DIRECTIONS FOR USE OF THE BAXTER STERILE CONTAINER SYSTEM

Guidelines for Preparation of Slush

The following instructions are intended only as guidelines for the preparation of slush using the Baxter Sterile Container System. The specific procedure necessary to achieve the desired slush consistency will depend on the type of freezer used, location of the product in the freezer, and the utilization of freezer capacity.

1. Remove product from shipping carton and place in freezer at a temperature between minus 4ºC and minus 15ºC for 2 to 6 hours. Note: A pre-cooled product will require less time to slush.
2. During the freezing process, remove product from freezer periodically and carefully massage to break up large frozen chunks of solution.
3. Return product to freezer and repeat procedure until desired slush consistency is obtained.

To Open: Use Aseptic Technique

A. To prepare unit outside the surgical field.

1. Tear overwrap down side at slit and remove dispensing bag which contains the slush container.
2. Allow unit to stand at room temperature for approximately 10 minutes to allow container material to regain flexibility.
3. Check that all the seals of the dispensing bag are intact including the tamper evident button. If any broken seals or holes are detected, discard unit as sterility may be impaired.
4. Grasp tab of dispensing bag and peel open (Figure 1). Remove wrapped inner slush container.
5. Grasp point of sterile transfer wrap (Figure 2), and pull forward then back to expose sterile slush container (Figure 3). Caution should be exercised to avoid touch contamination.

B. To transfer sterile slush container to the surgical field.

1. Using sterile gloved hands, remove slush container from the sterile transfer wrap (Figure 4). Place on surgical field or use immediately.
2. Grasp tab at top of slush container and peel directly across the width of the container with a steady motion (Figure 5).
3. Slush is ready for dispensing.

Baxter Healthcare Corporation
Deerfield, IL 60015 USA

Printed in USA

Distributed in Canada by
Baxter Corporation
Mississauga, ON L5N OC2

07-19-00-0323
Rev. April 2018

Baxter is a registered trademark of Baxter International Inc.

PRINCIPAL DISPLAY PANEL - PACKAGING LABELING

1000 mL
2B7231

NDC 0338-0051-44
Din 00786160

NOT FOR INJECTION

0.9% Sodium Chloride
Irrigation, USP
Baxter Sterile Container System

EACH 100 mL CONTAINS 900 mg SODIUM CHLORIDE
USP pH 5.0 (4.5 TO 7.0) mEq/L SODIUM 154
CHLORIDE 154 OSMOLARITY 308 mOsmol/L (CALC)
STERILE NONPYROGENIC SINGLE DOSE CONTAINER

FOR USE ONLY IN SLUSH PREPARATION
FOR REGIONAL HYPOTHERMIA

SEE ACCOMPANYING DIRECTIONS FOR USE
DOSAGE AS DIRECTED BY A PHYSICIAN
CAUTION RX ONLY

Baxter Logo
Baxter Healthcare Corporation
Deerfield IL 60015 USA

Made in USA

Distributed in Canada by
Baxter Corporation
Misissauga ON L5N 0C2

PL 146 Plastic

Baxter and PL 146 are trademarks of Baxter International Inc